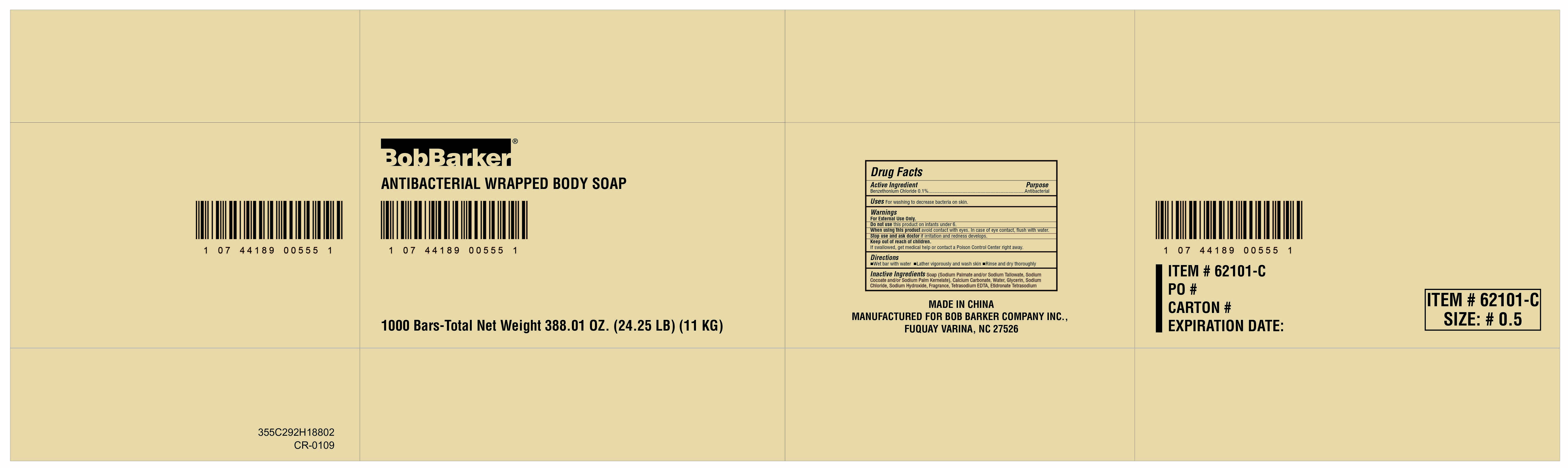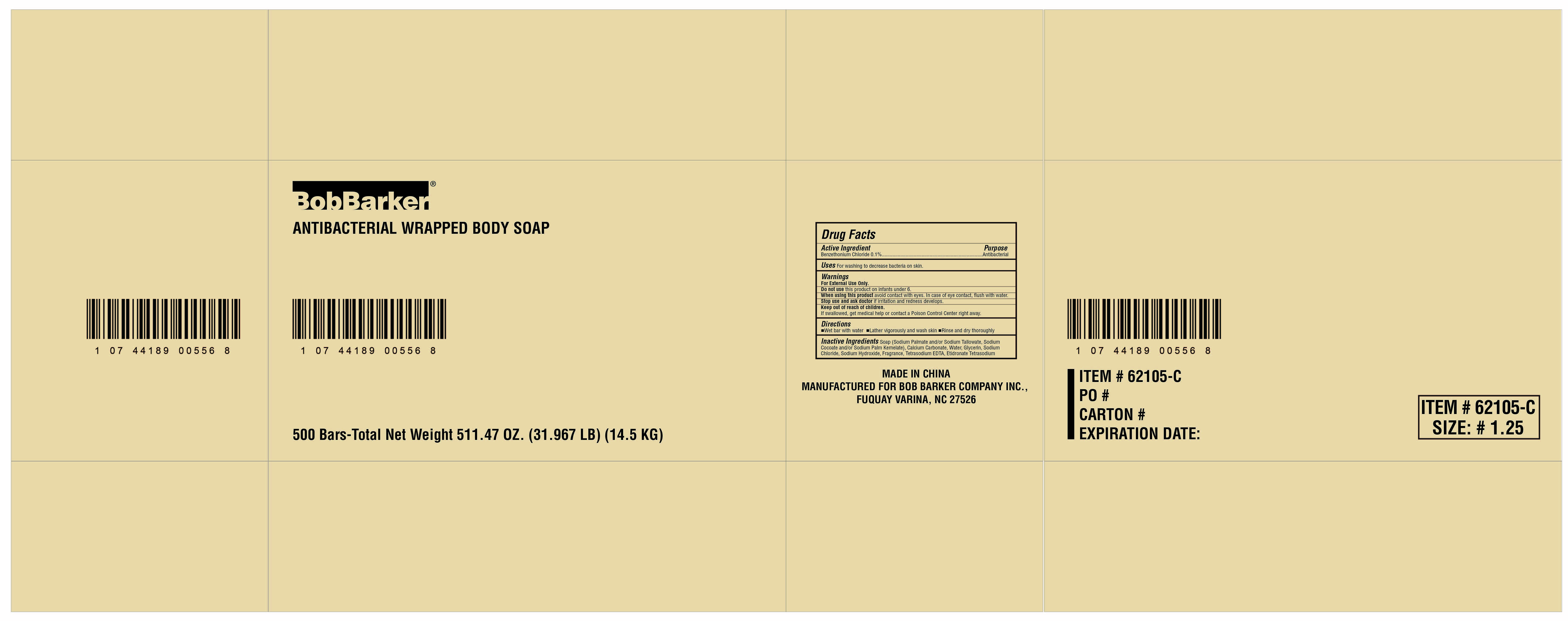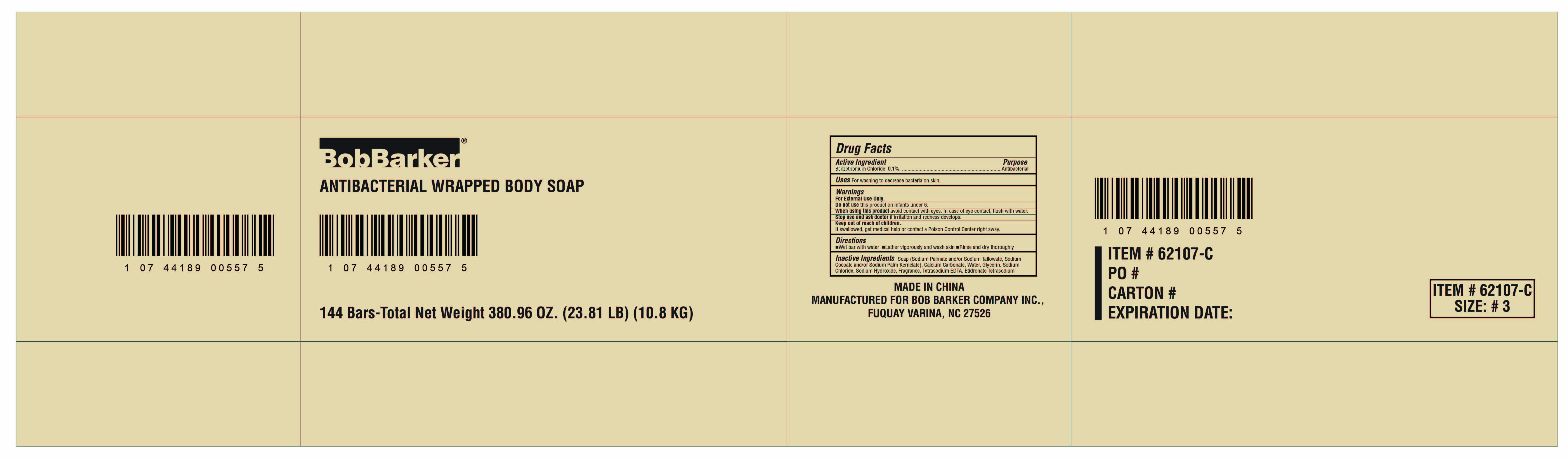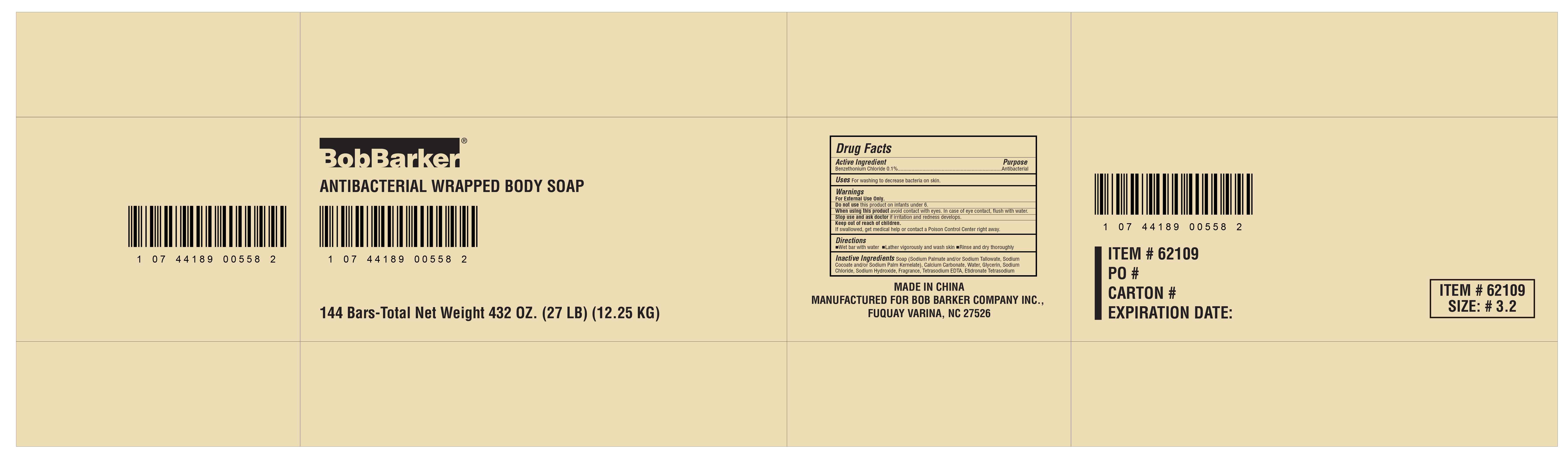 DRUG LABEL: Bob Barker Antibacterial Wrapped Body
NDC: 73027-201 | Form: SOAP
Manufacturer: JIANGSU HANHE DAILY CHEMICALS CO., LTD.
Category: otc | Type: HUMAN OTC DRUG LABEL
Date: 20211102

ACTIVE INGREDIENTS: BENZETHONIUM CHLORIDE 0.1 g/100 g
INACTIVE INGREDIENTS: SODIUM PALMATE; SODIUM TALLOWATE, BEEF; SODIUM COCOATE; SODIUM PALM KERNELATE; CALCIUM CARBONATE; WATER; GLYCERIN; SODIUM CHLORIDE; SODIUM HYDROXIDE; TRISODIUM HEDTA; ETIDRONATE TETRASODIUM

Active Ingredient:
Benzethonium Chloride: 0.1%

Purpose:

Antibacterial

Uses:

For washing to decrease bacteria on skin

Warnings:

For external use only

Do not use this product on infants under six

When using this product, avoid contact with eyes. In case of eye contact, fush with water

Stop use and ask doctor if irritation and redness develop

Do not use this product on infants under age of 6

Keep out of reach of children. If swallowed, get medical help or contact a Poison Control Center right away.

DOSAGE AND ADMINISTRATION

Wet bar with water

Lather vigorously and wash skin

Rinse and dry thoroughly

Inactive Ingredients:

Soap (Sodium Palmate, and/or Sodium Tallowate, Sodium Cocoate, and/or Sodium Palm Kernelate), Calcium Carbonate, Water, Glycerin, Sodium Chloride, Sodium Hydroxide, Fragrance, Tetrasodium EDTA, Etidronate Tetrasodium